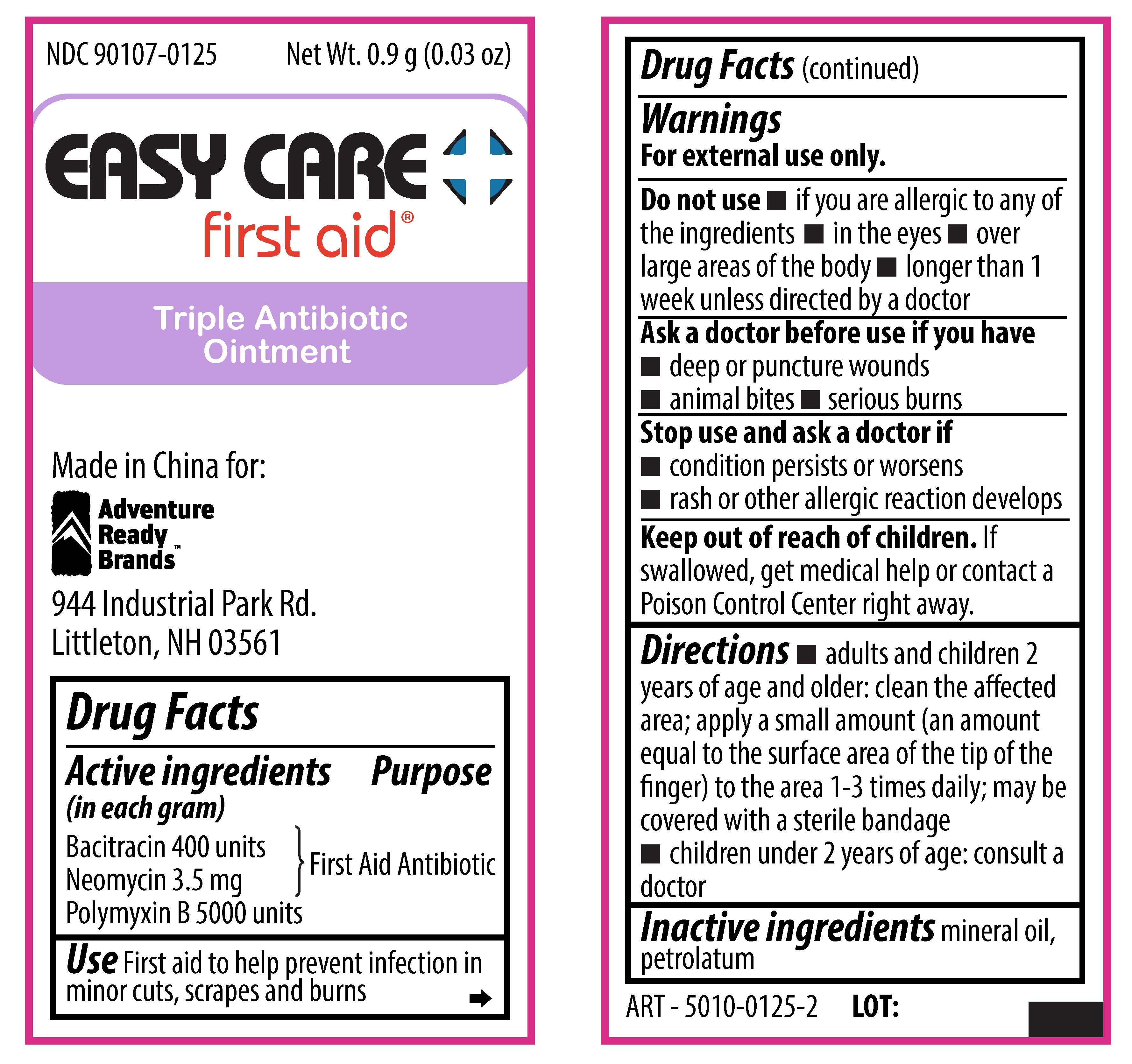 DRUG LABEL: Easy Care First Aid Triple Antibiotic
NDC: 90107-0125 | Form: OINTMENT
Manufacturer: Adventure Ready Brands
Category: otc | Type: HUMAN OTC DRUG LABEL
Date: 20201210

ACTIVE INGREDIENTS: BACITRACIN ZINC 400 [iU]/1 g; NEOMYCIN SULFATE 5 mg/1 g; POLYMYXIN B SULFATE 5000 [iU]/1 g
INACTIVE INGREDIENTS: PETROLATUM; MINERAL OIL

Easy Care First Aid Triple Antibiotic

Active Ingredients

Bacitracin Zinc 400 units

Neomycin Sulfate 5mg (equivalent to 3.5 mg Neomycin base)

Polymyxin B Sulfate 5000 units

Purpose

First Aid Antibiotic

Use

First aid to help prevent infection in minor cuts, scrapes, and burns

Warnings

For external use only.

Do not use

- if you are allergic to any of the ingredients
- in the eyes
- over large areas of the body

Ask a doctor before use if you have

- deep puncture wounds
- animal bites
- serious burns

Stop use and ask a doctor if

Symptoms persist for more than 7 days or clear up and occur again within a few days.

Keep out of Reach of Children

if swallowed, get medical help or contact a Poison Control Center right away

Directions

- adults and children 2 year of age and older: clean the affected area; apply a small amount to the area 1-3 times daily; may be covered with a sterile bandage
- children under 2 years of age: consult a doctor

Inactive Ingredients

mineral oil, petrolatum